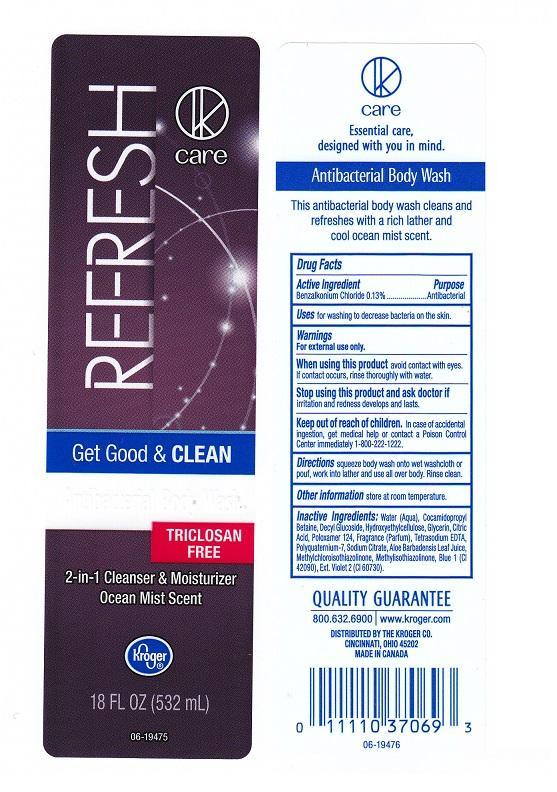 DRUG LABEL: K CARE
NDC: 30142-802 | Form: LIQUID
Manufacturer: THE KROGER COMPANY
Category: otc | Type: HUMAN OTC DRUG LABEL
Date: 20140411

ACTIVE INGREDIENTS: BENZALKONIUM CHLORIDE 1.3 mg/1 mL
INACTIVE INGREDIENTS: WATER; COCAMIDOPROPYL BETAINE; DECYL GLUCOSIDE; HYDROXYETHYL CELLULOSE (5000 CPS AT 1%); GLYCERIN; CITRIC ACID MONOHYDRATE; POLOXAMER 124; EDETATE SODIUM; POLYQUATERNIUM-7 (70/30 ACRYLAMIDE/DADMAC; 1600000 MW); SODIUM CITRATE; ALOE VERA LEAF; METHYLCHLOROISOTHIAZOLINONE; METHYLISOTHIAZOLINONE; FD&C BLUE NO. 1; D&C VIOLET NO. 2

DRUG FACTS

ACTIVE INGREDIENT

BENZALKONIUM CHLORIDE 0.13%

PURPOSE

ANTIBACTERIAL

USES

FOR WASHING TO DECREASE BACTERIA ON THE SKIN

WARNINGS

FOR EXTERNAL USE ONLY

WHEN USING THIS PRODUCT

AVOID CONTACT WITH EYES. IF CONTACT OCCURS, RINSE THOROUGHLY WITH WATER

STOP USING THIS PRODUCT AND ASK DOCTOR IF

IRRITATION AND REDNESS DEVELOPS AND LASTS

KEEP OUT OF REACH OF CHILDREN

IN CASE OF ACCIDENTAL INGESTION, GET MEDICAL HELP OR CONTACT A POISON CONTROL CENTER IMMEDIATELY 1-800-222-1222

DIRECTIONS

SQUEEZE BODY WASH ONTO WET WASHCLOTH OR POUF, WORK INTO LATHER AND USE ALL OVER BODY. RINSE CLEAN

OTHER INFORMATION

STORE AT ROOM TEMPERATURE

INACTIVE INGREDIENTS

WATER (AQUA), COCAMIDOPROPYL BETAINE, DECYL GLUCOSIDE, HYDROXYETHYLCELLULOSE, GLYCERIN, CITRIC ACID, POLOXAMER 124, FRAGRANCE (PARFUM), TETRASODIUM EDTA, POLYQUATERNIUM-7, SODIUM CITRATE, ALOE BARBADENSIS LEAF JUICE, METHYLCHLOROISOTHIAZOLINONE, METHYLISOTHIAZOLINONE, BLUE 1 (CI 42090), EXT. VIOLET 2 (CI 60730)